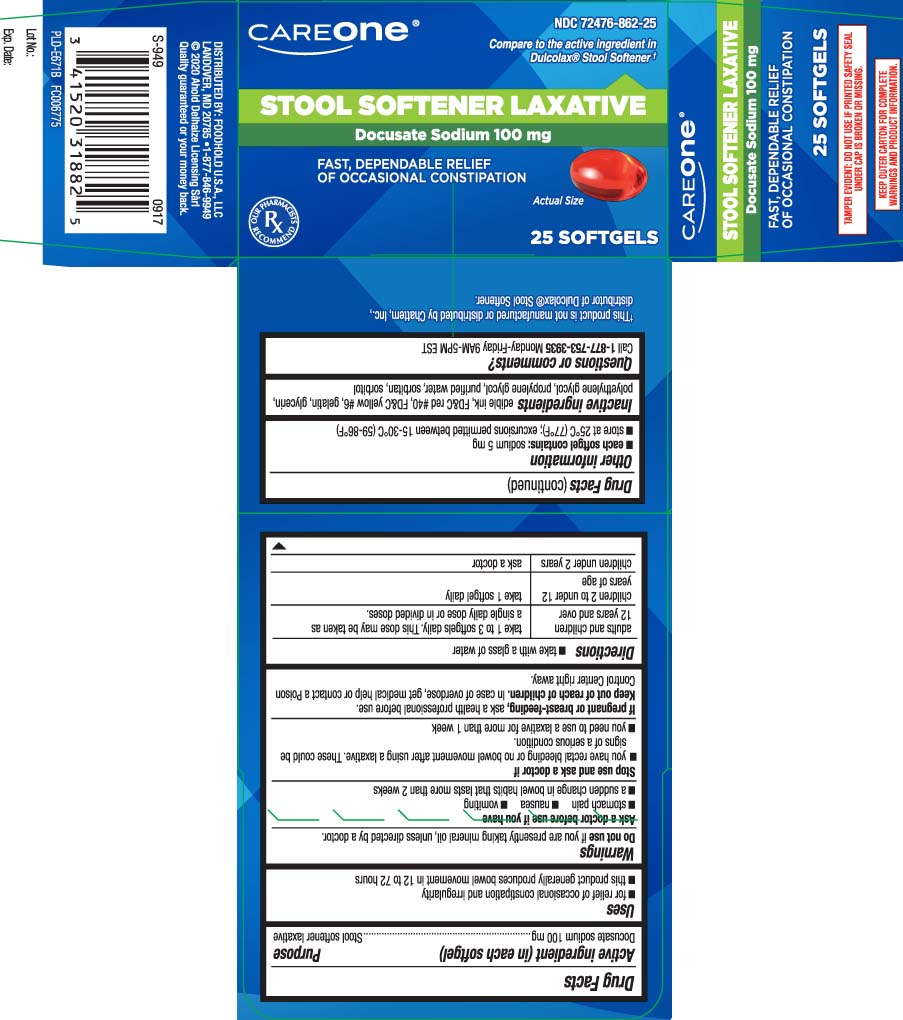 DRUG LABEL: Stool Softener Laxative
NDC: 72476-862 | Form: CAPSULE
Manufacturer: Care One (Retail Business Services, LLC.)
Category: otc | Type: HUMAN OTC DRUG LABEL
Date: 20240305

ACTIVE INGREDIENTS: DOCUSATE SODIUM 100 mg/1 1
INACTIVE INGREDIENTS: FD&C RED NO. 40; FD&C YELLOW NO. 6; GELATIN; GLYCERIN; POLYETHYLENE GLYCOL, UNSPECIFIED; PROPYLENE GLYCOL; WATER; SORBITOL; SORBITAN

Drug Facts

Active Ingredient (in each softgel)

Docusate Sodium 100 mg

Purpose

Stool softener laxative

Purpose

Stool Softener Laxative

Uses

- for relief of occasional constipation and irregularity
- this product generally produces a bowel movement in 12 to 72 hours.

Warnings

Do not use

if you are presently taking mineral oil, unless directed by a doctor

Ask a doctor before use if you have

- stomach pain
- nausea
- vomiting
- a sudden change in bowel habits that lasts more than 2 weeks

Stop use and ask a doctor if

- you have rectal bleeding or no bowel movement after using laxative. These could be signs of a serious condition.
- you need to use a laxative for more than 1 week

If pregnant or breast-feeding,

ask a health care professional before use.

Keep out of reach of children.

In case of overdose, get medical help or contact a Poison Control Center right away.

Directions

- take with a glass of water

adults and children 12 years and over | take 1 to 3 softgels daily. This dose may be taken as a single daily dose or in divided doses.
children 2 to under 12 years of age | take 1 softgel daily
children under 2 years of age | ask a doctor

Other information

- each softgel contains: sodium 5 mg
- store at 25oC (77o); excursions permitted between 15-30oC (59-86oF)

Inactive Ingredients

edible ink, FD&C Red #40, FD&C Yellow #6, gelatin, glycerin, polyethylene glycol, propylene glycol, purified water, sorbitan, sorbitol

Questions or Comments ?

Call 1-877-753-3935 Monday- Friday 9AM- 5PM EST

Principal Display Panel

Compare to the active ingredient in Dulcolax® Stool Softener†

STOOL SOFTENER LAXATIVE

Docusate Sodium 100 mg

FAST, DEPENDABLE RELIEF OF OCCASIONAL CONSTIPATION

SOFTGELS

TAMPER EVIDENT: DO NOT USE IF PRINTED SAFETY SEAL UNDER CAP IS BROKEN OR MISSING

KEEP OUTER CARTON FOR COMPLETE WARNINGS AND PRODUCT INFORMATION

DISTRIBUTED BY FOODHOLD U.S.A., LLC

LANDOVER, MD 20785

Product Label

CAREONE Stool Softener Laxative